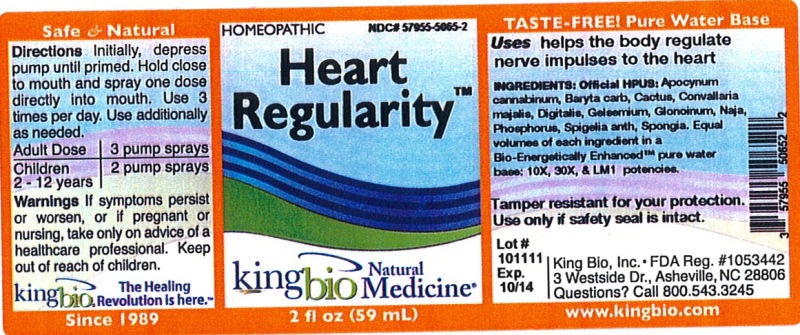 DRUG LABEL: Heart  Regularity
NDC: 57955-5065 | Form: LIQUID
Manufacturer: King Bio Inc.
Category: homeopathic | Type: HUMAN OTC DRUG LABEL
Date: 20120621

ACTIVE INGREDIENTS: APOCYNUM CANNABINUM ROOT 10 [hp_X]/59 mL; BARIUM CARBONATE 10 [hp_X]/59 mL; SELENICEREUS GRANDIFLORUS STEM 10 [hp_X]/59 mL; CONVALLARIA MAJALIS 10 [hp_X]/59 mL; CYPRIPEDIUM PARVIFOLUM ROOT 10 [hp_X]/59 mL; GELSEMIUM SEMPERVIRENS ROOT 10 [hp_X]/59 mL; NITROGLYCERIN 10 [hp_X]/59 mL; NAJA NAJA VENOM 10 [hp_X]/59 mL; PHOSPHORUS 10 [hp_X]/59 mL; SPIGELIA ANTHELMIA 10 [hp_X]/59 mL; SPONGIA OFFICINALIS SKELETON, ROASTED 10 [hp_X]/59 mL
INACTIVE INGREDIENTS: WATER

Heart Regularity

Active Ingredients

Official HPUS: Apocynum cannabinum, Baryta carbonica, Cactus grandiflorus, Convallaria majalis, Cypripedium pubescens, Gelsemium sempervirens, Glonoinum, Naja tripudians, Phosphorus, Spigelia anthelmia and Spongia tosta.

Reference image heart.jpg

Inactive Ingredient

Equal volumes of each ingredient in a Bio-Energetically Enhanced pure water base: 10X, 30X and LM1 potencies.

Reference image heart.jpg

Purpose

- Uses helps the body regulate nerve impulses to the heart.

Reference image heart.jpg

Dosage and Administration

Directions: Initially, depress pump until primed. Hold close to mouth and spray one dose directly into mouth. Use 3 times per day Use additionally as needed.

Adult Dose 3 pump sprays

Children 2-12 years 2 pump sprays

Reference image heart.jpg

Warnings

If symptoms persist or worsen, or if pregnant or nursing, take only on advice of a healthcare professional. Keep out of reach of children.

Other: Tamper resistant for your protection. Use only if safety seal is intact.

Reference image heart.jpg

Keep out of reach of children.

Reference image heart.jpg

Indications and Usage

Uses helps the body regulate nerve impulses to the heart.

Reference image heart.jpg

PACKAGE LABEL

King Bio Inc.

3 Westside Drive

Asheville, NC 28806

Question? Call 800.543.3245

www.kingbio.com